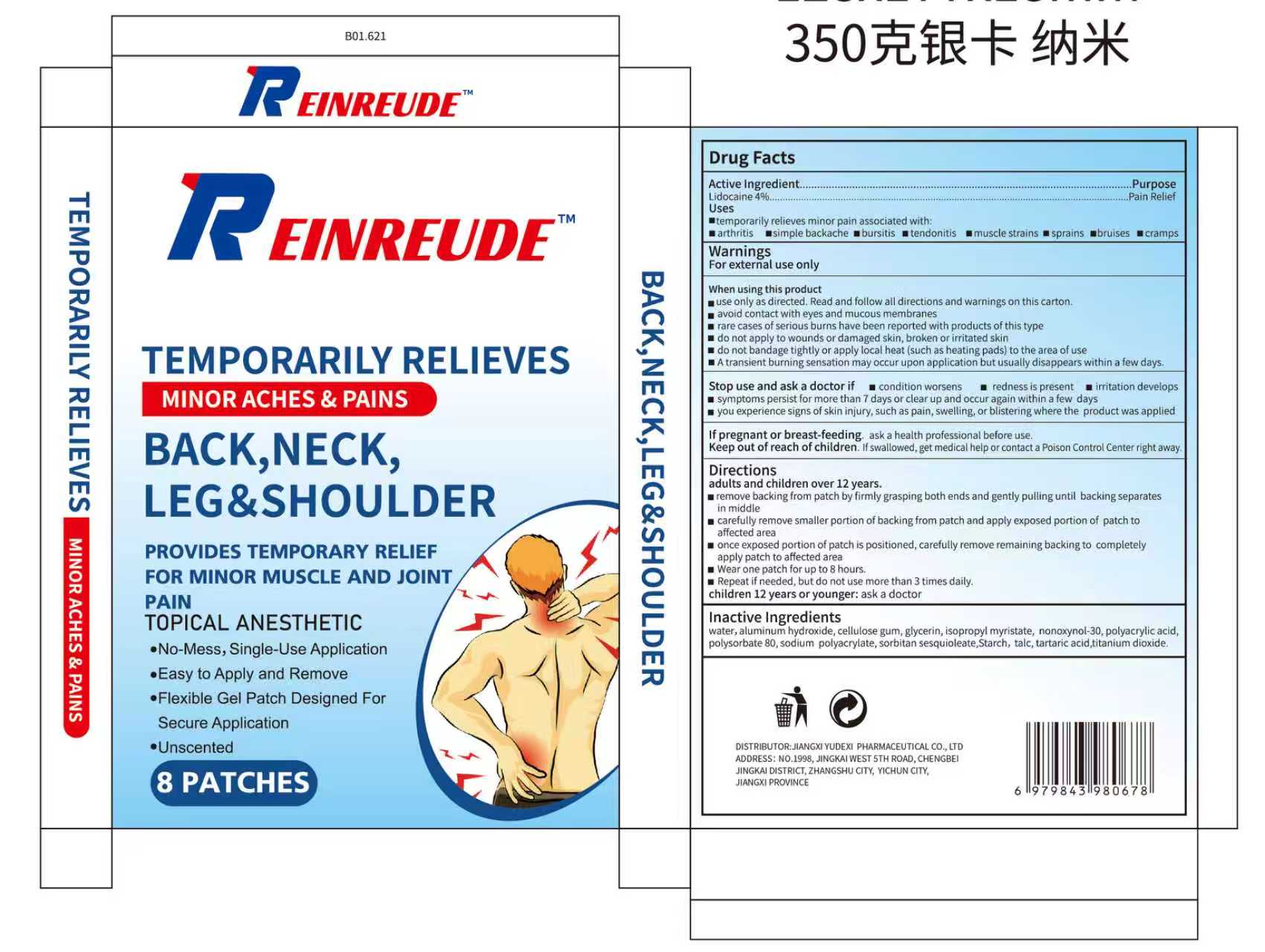 DRUG LABEL: REINREUDE PROVIDES TEMPORARY RELIEF FOR MINOR MUSCLE AND JOINT PAIN
NDC: 85248-076 | Form: PATCH
Manufacturer: Jiangxi Yudexi Pharmaceutical Co., LTD
Category: otc | Type: HUMAN OTC DRUG LABEL
Date: 20260207

ACTIVE INGREDIENTS: LIDOCAINE 4 g/100 1
INACTIVE INGREDIENTS: SORBITAN SESQUIOLEATE; ISOPROPYL MYRISTATE; TITANIUM DIOXIDE; ALUMINUM HYDROXIDE; GLYCERIN; NONOXYNOL-30; POLYSORBATE 80; TARTARIC ACID; WATER; CELLULOSE GUM; SODIUM POLYACRYLATE (2500000 MW); STARCH, CORN; TALC; POLYACRYLIC ACID (250000 MW)

85248-076

Active Ingredient

Lidocaine 4%

Purpose

Pain Relief

Use

▆temporarily relieves minor pain associated with: ▆arthritis ▆simple backache▆bursitis ▆tendonitis ▆muscle strains ▆sprains▆bruises ▆cramps

Warnings

For external use only

Do not use

▆use only as directed. Read and follow all directions and warnings on this carton. ▆avoid contact with eyes and mucous membranes ▆rare cases of serious burns have been reported with products of this type ▆ do not apply to wounds or damaged skin, broken or irritated skin ▆do not bandage tightly or apply local heat (such as heating pads) to the area of use ▆ A transient burning sensation may occur upon application but usually disappears within a few days.

When Using

▆use only as directed. Read and follow all directions and warnings on this carton. ▆avoid contact with eyes and mucous membranes ▆rare cases of serious burns have been reported with products of this type ▆ do not apply to wounds or damaged skin, broken or irritated skin ▆do not bandage tightly or apply local heat (such as heating pads) to the area of use ▆ A transient burning sensation may occur upon application but usually disappears within a few days.

Stop Use

▆condition worsens ▆redness is present ▆irritation develops▆symptoms persist for more than 7 days or clear up and occur again within a few dsys ▆you experience signs of skin injury, such as pain, swelling, or blistering where the product was applied If pregnant or breast-feeding. ask a health professional before use

Ask Doctor

▆condition worsens ▆redness is present ▆irritation develops▆symptoms persist for more than 7 days or clear up and occur again within a few dsys ▆you experience signs of skin injury, such as pain, swelling, or blistering where the product was applied

Keep Oot Of Reach Of Children

Keep out of reach of children. lf swallowed, get medical help or contact a Poison Control Center right away

Directions

adults and children over 12 years. ▆remove backing from patch by firmly grasping both ends and gently pulling until backing separate in middle ▆carefully remove smaller portion of backing from patch and apply exposed portion of patch to affected area ▆once exposed portion of patch is positioned, carefully remove remaining backing to completely apply patch to affected area ▆Wear one patch for up to 8 hours. ▆Repeat if needed, but do not use more than 3 times daily. children 12 years or younger: ask a doctor

Inactive ingredients

water, aluminym hvdroxide, cellulose gum, glvcerin, isopropyl myristate, nonoxynol-30, polyacrylic aciopolysorbate 80, sodium polvacrvlate, sorbitan sesauioleate,Starch, talc, tartaric acid,titanium dioxide